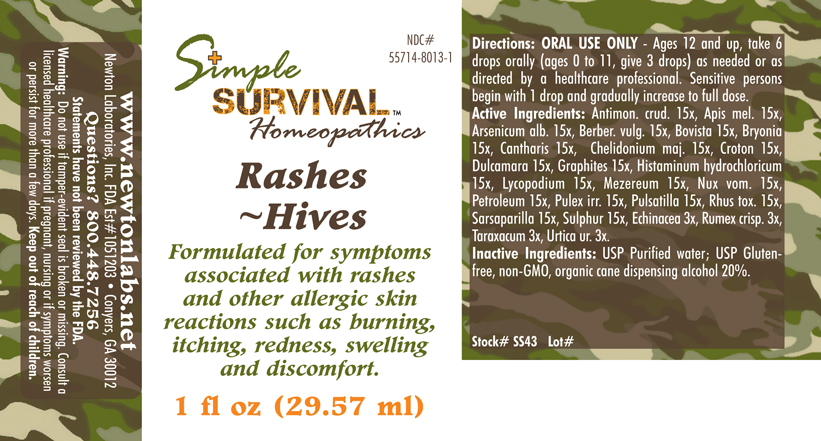 DRUG LABEL: Rashes - Hives 
NDC: 55714-8013 | Form: LIQUID
Manufacturer: Newton Laboratories, Inc.
Category: homeopathic | Type: HUMAN OTC DRUG LABEL
Date: 20140415

ACTIVE INGREDIENTS: Antimony Trisulfide 15 [hp_X]/1 mL; Apis Mellifera 15 [hp_X]/1 mL; Arsenic Trioxide 15 [hp_X]/1 mL; Berberis Vulgaris Root Bark 15 [hp_X]/1 mL; Giant Puffball 15 [hp_X]/1 mL; Bryonia Alba Root 15 [hp_X]/1 mL; Lytta Vesicatoria 15 [hp_X]/1 mL; Chelidonium Majus 15 [hp_X]/1 mL; Croton Tiglium Seed 15 [hp_X]/1 mL; Solanum Dulcamara Top 15 [hp_X]/1 mL; Graphite 15 [hp_X]/1 mL; Histamine Dihydrochloride 15 [hp_X]/1 mL; Lycopodium Clavatum Spore 15 [hp_X]/1 mL; Daphne Mezereum Bark 15 [hp_X]/1 mL; Strychnos Nux-vomica Seed 15 [hp_X]/1 mL; Kerosene 15 [hp_X]/1 mL; Pulex Irritans 15 [hp_X]/1 mL; Pulsatilla Vulgaris 15 [hp_X]/1 mL; Toxicodendron Pubescens Leaf 15 [hp_X]/1 mL; Smilax Regelii Root 15 [hp_X]/1 mL; Sulfur 15 [hp_X]/1 mL; Echinacea, Unspecified 3 [hp_X]/1 mL; Rumex Crispus Root 3 [hp_X]/1 mL; Taraxacum Officinale 3 [hp_X]/1 mL; Urtica Urens 3 [hp_X]/1 mL
INACTIVE INGREDIENTS: Alcohol

Rashes - Hives

INDICATIONS & USAGE SECTION

Rashes - Hives Formulated for symptoms associated with rashes and other allergic skin reactions such as burning, itching, redness, swelling and discomfort.

DOSAGE & ADMINISTRATION SECTION

Directions: ORAL USE ONLY - Ages 12 and up, take 6 drops orally (ages 0 to 11, give 3 drops) as needed or as directed by a healthcare professional. Sensitive persons begin with 1 drop and gradually increase to full dose.

OTC - ACTIVE INGREDIENT SECTION

Antimon. crud. 15x, Apis mel. 15x, Arsenicum alb. 15x, Berber. vulg. 15x, Bovista 15x, Bryonia 15x, Cantharis 15x, Chelidonium maj. 15x, Croton 15x, Dulcamara 15x, Graphites 15x, Histaminum hydrochloricum 15x, Lycopodium 15x, Mezereum 15x, Nux vom. 15x, Petroleum 15x, Pulex irr. 15x, Pulsatilla 15x, Rhus tox. 15x, Sarsaparilla 15x, Sulphur 15x, Echinacea 3x, Rumex crisp. 3x, Taraxacum 3x, Urtica ur. 3x.

OTC - PURPOSE SECTION

Formulated for symptoms associated with rashes and other allergic skin reactions such as burning, itching, redness, swelling and discomfort.

INACTIVE INGREDIENT SECTION

Inactive Ingredients: USP Purified Water; USP Gluten-free, non-GMO, organic cane dispensing alcohol 20%.

QUESTIONS SECTION

www.newtonlabs.net Newton Laboratories, Inc. FDA Est # 1051203 - Conyers, GA 30012
Questions? 1.800.448.7256

WARNINGS SECTION

Warning: Do not use if tamper - evident seal is broken or missing. Consult a licensed healthcare professional if pregnant, nursing or if symptoms worsen or persist for more than a few days. Keep out of reach of children.

OTC - PREGNANCY OR BREAST FEEDING SECTION

Consult a licensed healthcare professional if pregnant, nursing or if symptoms worsen or persist for more than a few days.

OTC - KEEP OUT OF REACH OF CHILDREN SECTION

Keep out of reach of children.